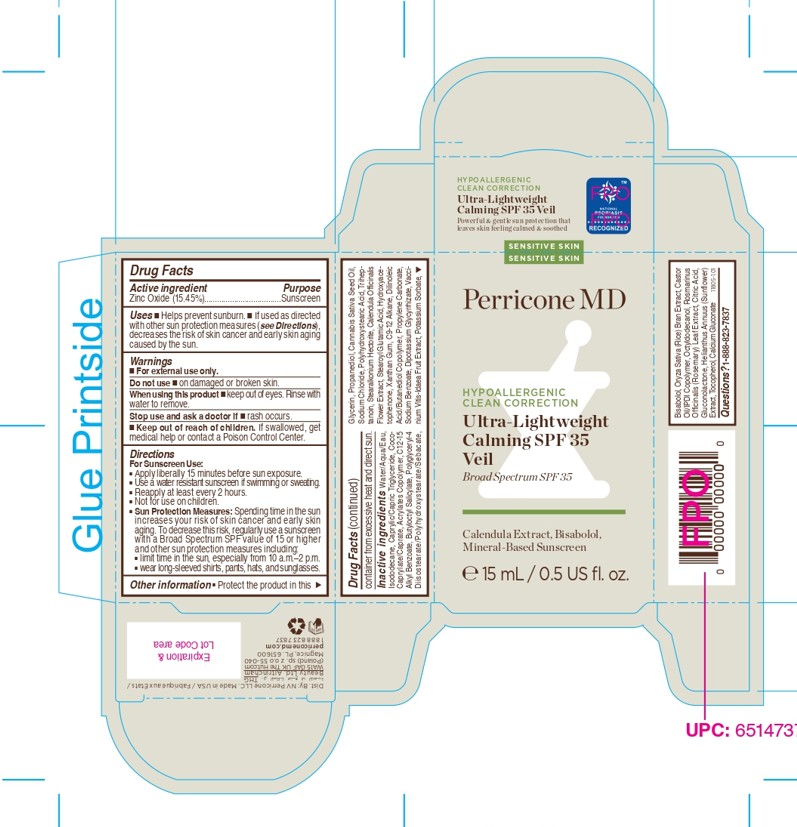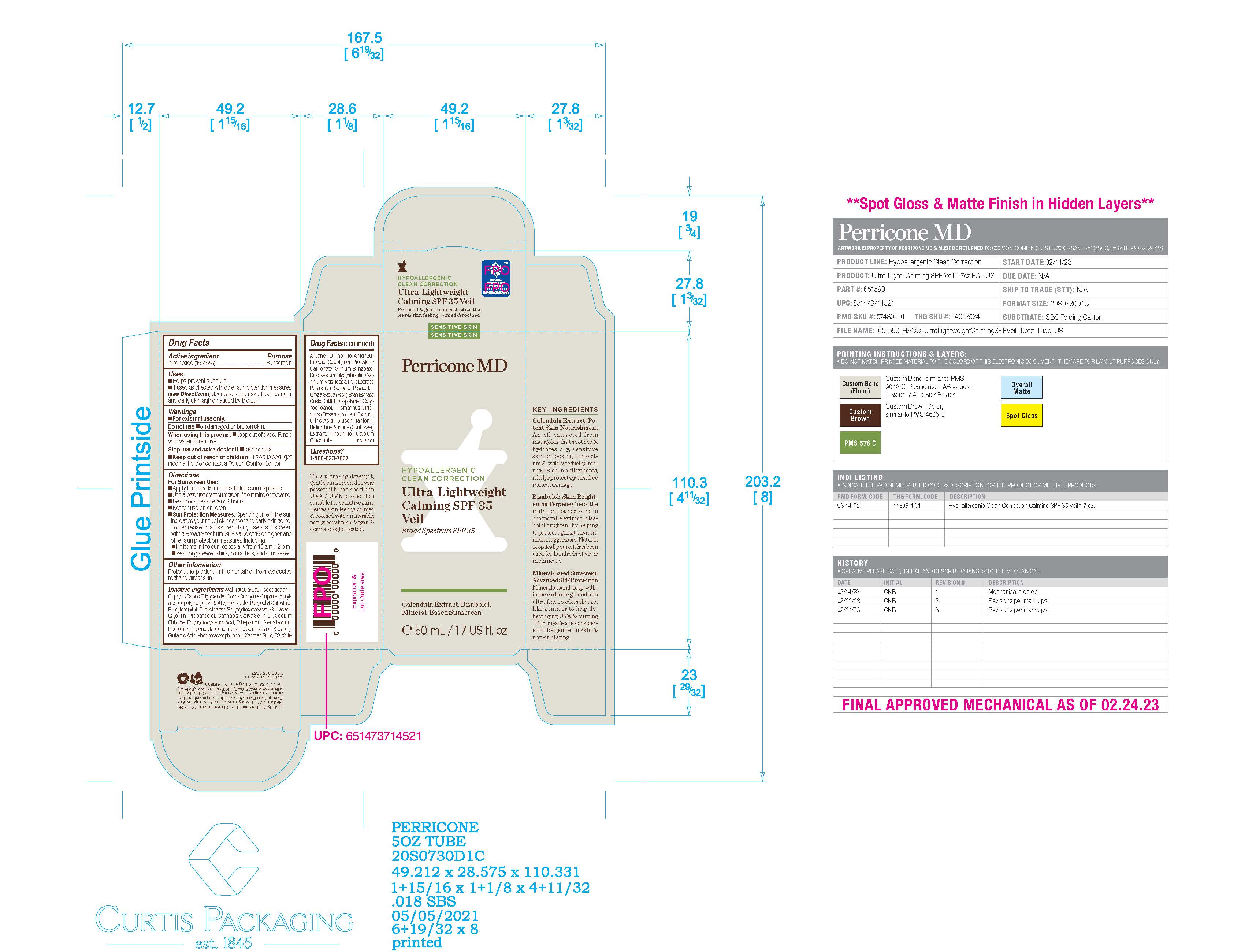 DRUG LABEL: Perricone MD Hypoallergenic Clean Correction Ultra-Lightweight Calming SPF 35 Veil
NDC: 84448-402 | Form: CREAM
Manufacturer: THG Beauty USA LLC
Category: otc | Type: HUMAN OTC DRUG LABEL
Date: 20251030

ACTIVE INGREDIENTS: ZINC OXIDE 15.45 g/100 mL
INACTIVE INGREDIENTS: BUTYLOCTYL SALICYLATE; TRIHEPTANOIN; CASTOR OIL/IPDI COPOLYMER; CITRIC ACID; CALENDULA OFFICINALIS FLOWER; DILINOLEIC ACID/BUTANEDIOL COPOLYMER; PROPYLENE CARBONATE; CALCIUM GLUCONATE; ISODODECANE; POLYHYDROXYSTEARIC ACID (2300 MW); STEAROYL GLUTAMIC ACID; HYDROXYACETOPHENONE; OCTYLDODECANOL; LINGONBERRY; CAPRYLIC/CAPRIC TRIGLYCERIDE; BUTYL ACRYLATE/METHYL METHACRYLATE/METHACRYLIC ACID COPOLYMER (18000 MW); BISABOLOL; ROSEMARY; C12-15 ALKYL BENZOATE; GLYCERIN; DIPOTASSIUM GLYCYRRHIZATE; PROPANEDIOL; CANNABIS SATIVA SEED OIL; GLUCONOLACTONE; HELIANTHUS ANNUUS FLOWERING TOP; WATER; XANTHAN GUM; TOCOPHEROL; COCO-CAPRYLATE/CAPRATE; POLYGLYCERYL-4 DIISOSTEARATE/POLYHYDROXYSTEARATE/SEBACATE; ORYZA SATIVA (RICE) BRAN; C9-12 ALKANE; POTASSIUM SORBATE; SODIUM CHLORIDE; STEARALKONIUM HECTORITE; SODIUM BENZOATE

ACTIVE INGREDIENT

Zinc Oxide 15.45%

PURPOSE

Sunscreen

INDICATIONS AND USAGE

Helps prevent sunburn

if used as directed with other sun protection measures (see directions), decreases the risk of skin cancer and early signs of aging caused by the sun.

WARNINGS

For external use only

Do not use on damaged or broken skin.

When using this product keep out of eyes. Rinse with water to remove.

Stop use and ask a doctor if rash occurs.

KEEP OUT OF REACH OF CHILDREN

If product is swallowed, get medical help or contact a Poison Control Centre right away.

Directions
For Sunscreen Use:
■ Apply liberally 15 minutes before sun exposure.
■ Use a water resistant sunscreen if swimming or sweating.
■ Reapply at least every 2 hours.
■ Not for use on children.
■ Sun Protection Measures: Spending time in the sun
increases your risk of skin cancer and early skin
aging. To decrease this risk, regularly use a sunscreen
with a Broad Spectrum SPF value of 15 or higher
and other sun protection measures including:
■ limit time in the sun, especially from 10 a.m.–2 p.m.
■ wear long-sleeved shirts, pants, hats, and sunglasses.

OTHER SAFETY INFORMATION

Protect the product in this container from excessive heat and direct sun

INACTIVE INGREDIENT

Water/Aqua/Eau, Isododecane, Caprylic/Capric Triglyceride, Coco-Caprylate/Caprate, Acrylates Copolymer, C12-15 Alkyl Benzoate, Butyloctyl Salicylate, Polyglyceryl-4 Diisostearate/Polyhydroxystearate/Sebacate, Glycerin, Propanediol, Cannabis Sativa Seed Oil, Sodium Chloride, Polyhydroxystearic Acid, Triheptanoin, Stearalkonium Hectorite, Calendula Officinalis Flower Extract, Stearoyl Glutamic Acid, Hydroxyacetophenone, Xanthan Gum, C9-12 Alkane, Dilinoleic Acid/Butanediol Copolymer, Propylene Carbonate, Sodium Benzoate, Dipotassium Glycyrrhizate, Vaccinium Vitis-Idaea Fruit Extract, Potassium Sorbate, Bisabolol, Oryza Sativa (Rice) Bran Extract, Castor Oil/IPDI Copolymer, Octyldodecanol, Rosmarinus Officinalis (Rosemary) Leaf Extract, Citric Acid, Gluconolactone, Helianthus Annuus (Sunflower) Extract, Tocopherol, Calcium Gluconate.

QUESTIONS

1-888-823-7837